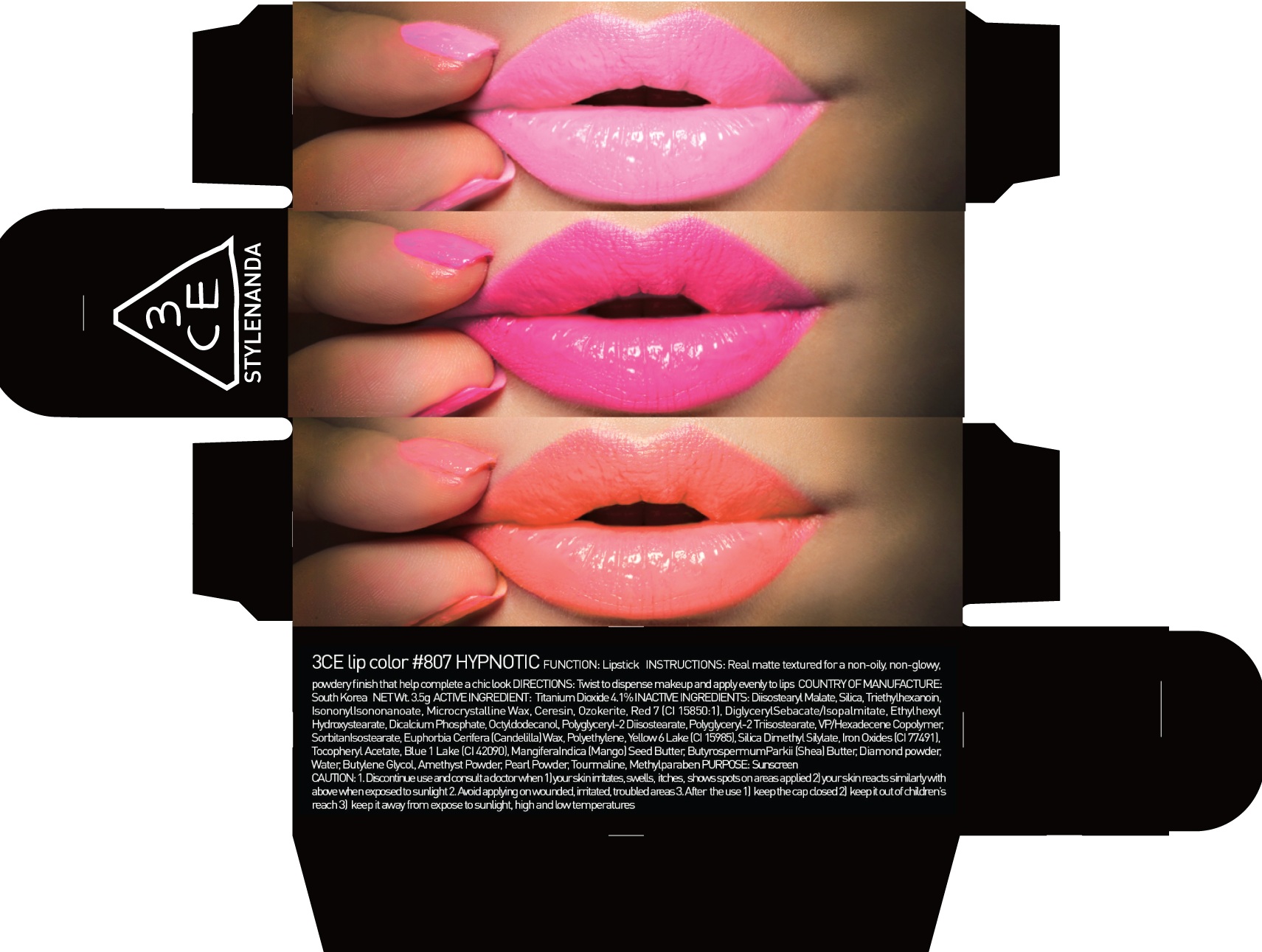 DRUG LABEL: 3CE LIP COLOR 807 HYPNOTIC
NDC: 60764-053 | Form: LIPSTICK
Manufacturer: Nanda Co., Ltd
Category: otc | Type: HUMAN OTC DRUG LABEL
Date: 20160930

ACTIVE INGREDIENTS: Titanium Dioxide 0.14 g/3.5 g
INACTIVE INGREDIENTS: Diisostearyl Malate; Triethylhexanoin

ACTIVE INGREDIENT

Active Ingredient: Titanium Dioxide 4.1%

INACTIVE INGREDIENT

Inactive Ingredients: Diisostearyl Malate, Silica, Triethylhexanoin, IsononylIsononanoate, Microcrystalline Wax, Ceresin, Ozokerite, Red 7 (CI 15850:1), DiglycerylSebacate/Isopalmitate, EthylhexylHydroxystearate, Dicalcium Phosphate, Octyldodecanol, Polyglyceryl-2 Diisostearate, Polyglyceryl-2 Triisostearate, VP/Hexadecene Copolymer, SorbitanIsostearate, Euphorbia Cerifera (Candelilla) Wax, Polyethylene, Yellow 6 Lake (CI 15985), Silica Dimethyl Silylate, Iron Oxides (CI 77491), Tocopheryl Acetate, Blue 1 Lake (CI 42090), MangiferaIndica (Mango) Seed Butter, ButyrospermumParkii (Shea) Butter, Diamond powder, Water, Butylene Glycol, Amethyst Powder, Pearl Powder, Tourmaline, Methylparaben

PURPOSE

Purpose: Sunscreen

CAUTION

CAUTION: 1. Discontinue use and consult a doctor when - your skin irritates, swells, itches, shows spots on areas applied - your skin reacts similarly with above when exposed to sunlight 2. Avoid applying on wounded, irritated, troubled areas 3. After the use - keep the cap closed - keep it out of children's reach - keep it away from expose to sunlight, high and low temperatures

DESCRIPTION

INSTRUCTIONS: A rich color lipstick that moistly adheres to lips.

Directions: Twist to dispense makeup and apply evenly to lips